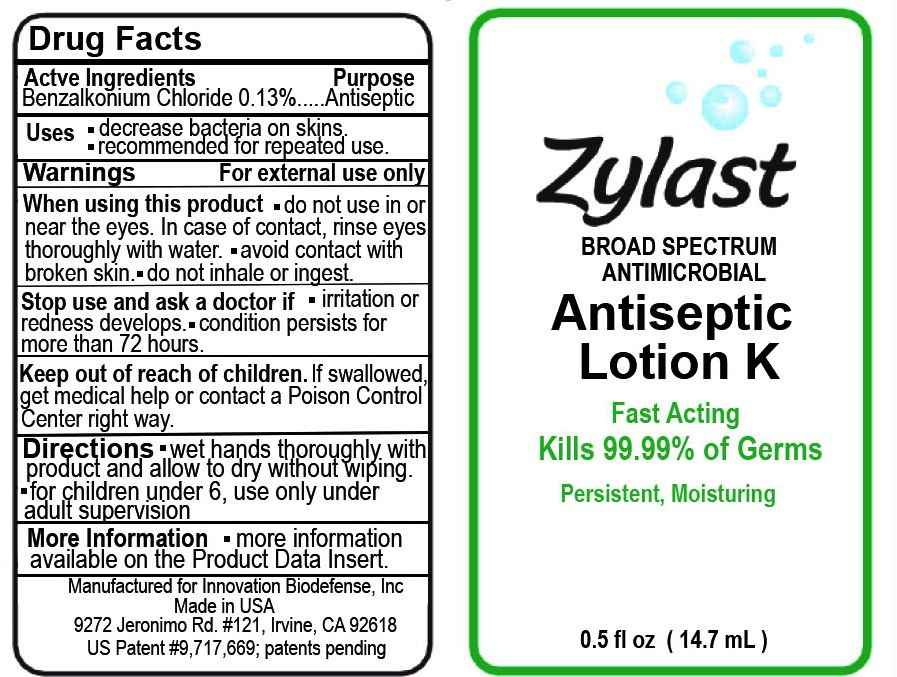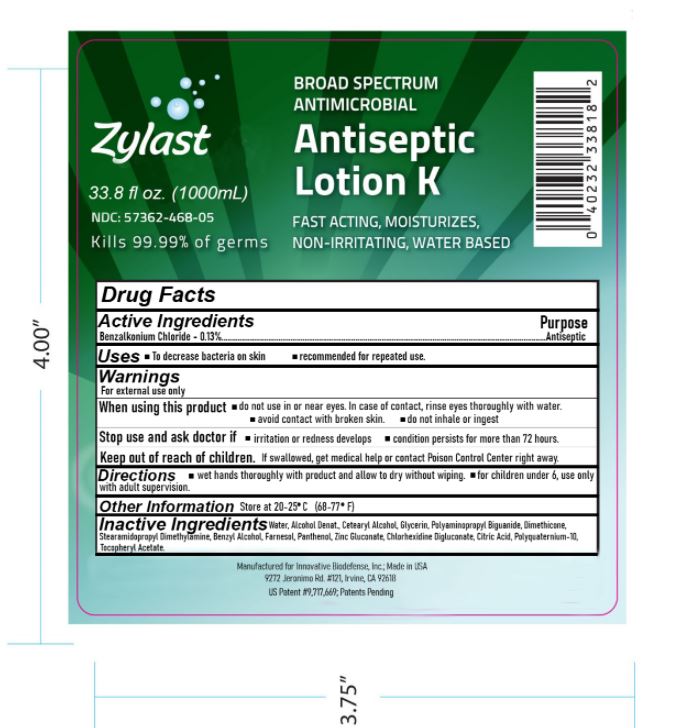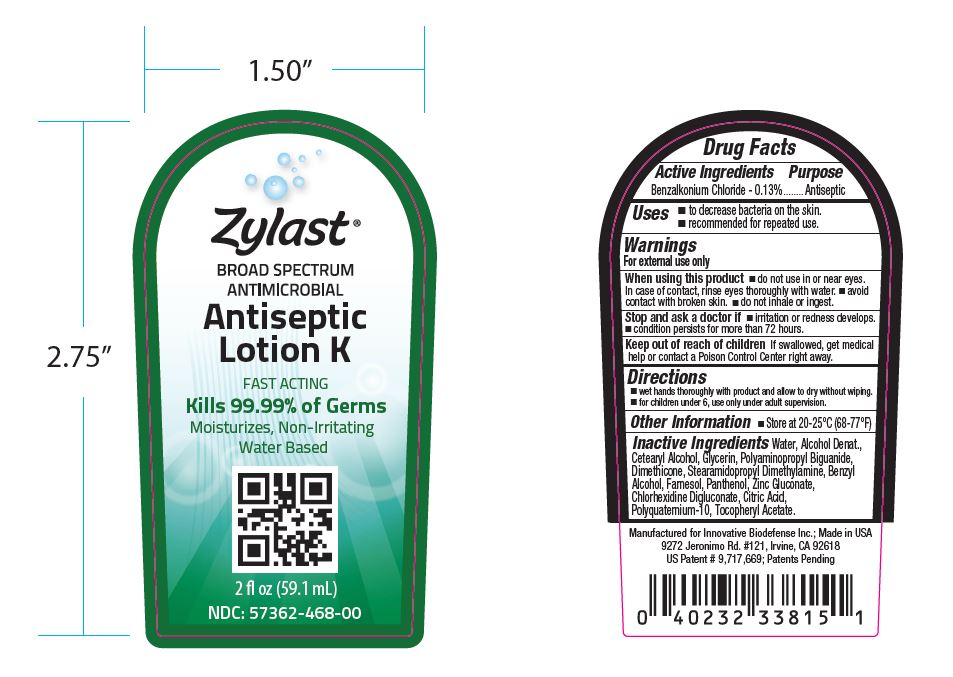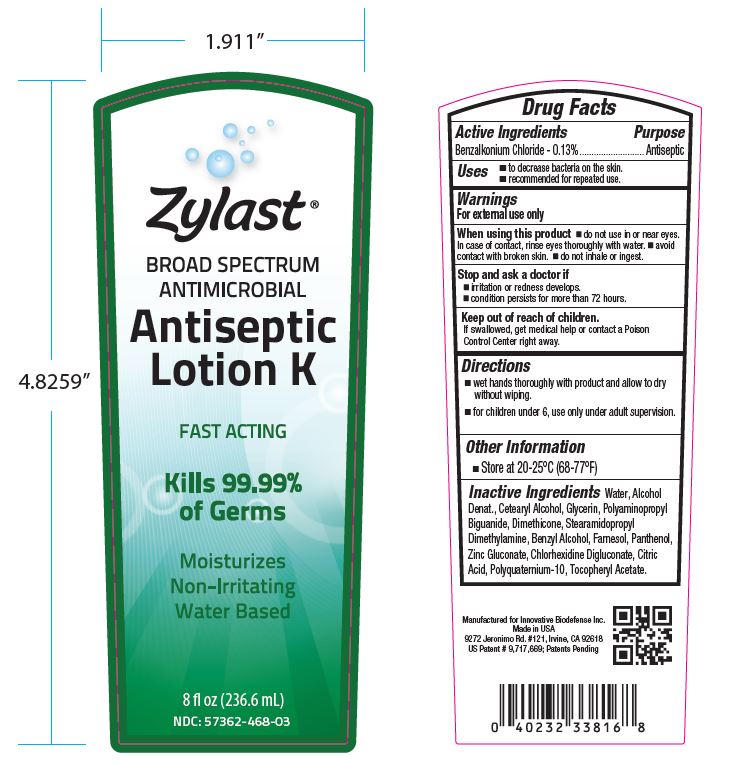 DRUG LABEL: Zylast Antiseptic K
NDC: 57362-468 | Form: LOTION
Manufacturer: Innovative Biodefense
Category: otc | Type: HUMAN OTC DRUG LABEL
Date: 20230101

ACTIVE INGREDIENTS: BENZALKONIUM CHLORIDE 0.13 g/100 mL
INACTIVE INGREDIENTS: WATER

Zylast Antiseptic
Lotion K

Active Ingredient

Benzalkonium Chloride- 0.13%

Purpose

Antiseptic

Uses

To decrease bacteria on skin. Recommended for repeated use.

Warnings

For external use only. When using this product, do not use in or near eyes. In case of contact, rinse eyes thoroughly with water. Avoid contact with broken skin. Do not inhale or ingest.

Keep Out of Reach of Children

If swallowed, get medical help or contact a poison control center right away.

Stop use and ask a doctor if

Irritation or redness develops. Condition persists for more than 72 hours.

Directions

Wet hands thoroughly with product and allow to dry without wiping. For children under 6, use only with adult supervision.

Inactive Ingredient

Water, Alcohol Denature, Cetearyl Alcohol, Glycerin,Phenoxyethanol Caprylyl Glycol Ethylhexylglycerin, Dimethicone, Stearamidopropyl Dimethylamine, Benzyl Alcohol, Farnesol, Panthenol, Zinc Gluconate, Chlorhexidine Digluconate, Citric Acid, Polyquaternium-10, Tocopheryl Acetate.

Other Information

Store at 20-25°C (68-77°F)

RECENT MAJOR CHANGES

- Uses section
- Warnings section
- Stop and ask a doctor if section
- Keep out of reach of children section
- Directions section
- Inactive Ingredient section
- Package Label. Principal Display Panel

PACKAGE LABEL

NDC 57362-468-04

Zylast

Broad Sprectrum

Antimicrobial

Antiseptic

14.79 mL (0.5 fl. oz)

NDC 57362-468-00

Zylast

Broad Sprectrum

Antimicrobial

Antiseptic

59.159 mL (2 fl. oz)

NDC 57362-468-03

Zylast

Broad Sprectrum

Antimicrobial

236.59 mL (8 fl. oz)

NDC 57362-468-05

Zylast

Broad Sprectrum

Antimicrobial

Antiseptic

1000 mL (33.8 fl. oz)